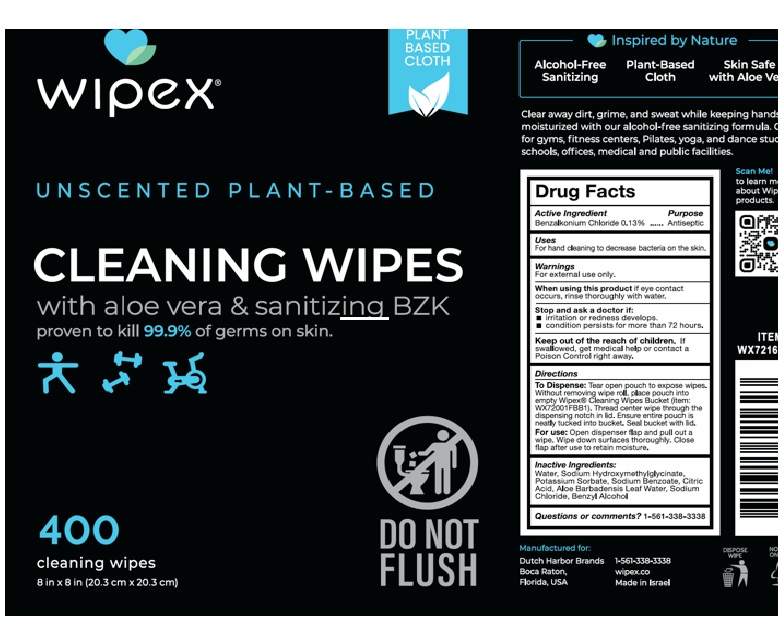 DRUG LABEL: Wipex Sanitizing Wipes
NDC: 74680-231 | Form: CLOTH
Manufacturer: Unico
Category: otc | Type: HUMAN OTC DRUG LABEL
Date: 20260102

ACTIVE INGREDIENTS: BENZALKONIUM CHLORIDE 1.3 mg/1 mL
INACTIVE INGREDIENTS: SODIUM BENZOATE; SODIUM CHLORIDE; SODIUM HYDROXYMETHYLGLYCINATE; ALOE VERA LEAF; POTASSIUM SORBATE; WATER; CITRIC ACID MONOHYDRATE

Wipex Sanitizing Wipes

Active Ingredient

Benzalkonium chloride 0.13%

Keep out of the reach of children. If swallowed, get medical help or contact a Poison Contrl right away.

Warnings

For external use only. Avoid cntact with the eyes. If in eyes, flush thoroughly with water.

Inactive ingredients

Sodium benzoate, sodium chloride, citric acid, potassium sorbate, sodium hydroxymethylglycinate, aloe vera leaf, water

Purpose

Antiseptic

Stop use if

Stop and ask a doctor if

- Irritation or redness developes.
- Conditions persists for more than 72 hours.

To use

Sanitize hands or other affected area. Discard in trash after use.

To dispense

To begin: Break tab on bucket rim and pull off cover. Open bag inside to expose wipes, then thread center wipe through the lid. Replace bucket cover to maintain moisture.